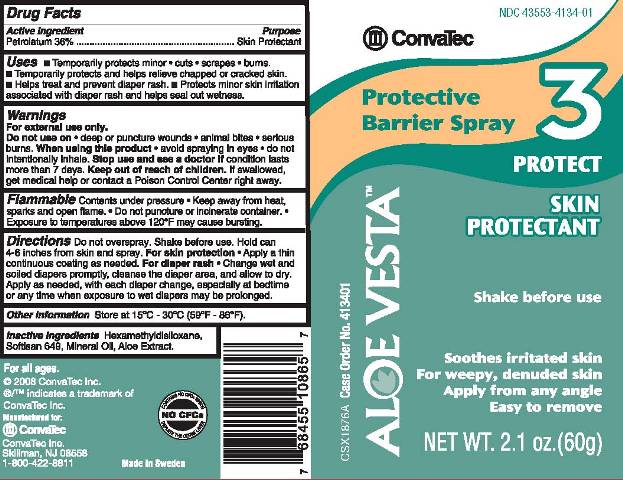 DRUG LABEL: ALOE VESTA PROTECTIVE BARRIER
NDC: 43553-4134 | Form: SPRAY
Manufacturer: ConvaTec, Inc.
Category: otc | Type: HUMAN OTC DRUG LABEL
Date: 20110408

ACTIVE INGREDIENTS: PETROLATUM 360 mg/1 g
INACTIVE INGREDIENTS: HEXAMETHYLDISILOXANE; MINERAL OIL; ALOE VERA LEAF

Drug Facts

Active Ingredient

Petrolatum 36%

Purpose

Skin Protectant

Uses

- Temporarily protects minor
- cuts
- scrapes
- burns.

- Temporarily protects and helps relieve chapped or cracked skin.
- Helps treat and prevent diaper rash.
- Protects minor skin irritation associated with diaper rash and helps seal out wetness.

Warnings

For external use only.

Do not use on

- deep or puncture wounds
- animal bites
- serious burns.

When using this product

- avoid spraying in eyes
- do not intentionally inhale.

Stop use and see a doctor if

condition lasts more than 7 days.

Keep out of reach of children.

If swallowed, get medical help or contact a Poison Control Center right away.

Flammable

Contents under pressure

- Keep away from heat, sparks, and open flame.
- Do not puncture or incinerate container.
- Exposure to temperatures above 120oF may cause bursting.

Directions

Do not overspray. Shake before use. Hold can 4-6 inches from skin and spray.

For skin protection

- Apply a thin continuous coating as needed.

For diaper rash

- Change wet and soiled diapers promptly, cleanse the diaper area, and allow to dry. Apply as needed, with each diaper change, especially at bedtime or any time when exposure to wet diapers may be prolonged.

Other Information

Store at 15oC - 30oC (59oF - 86oF).

Inactive Ingredients

Hexamethyldisiloxane, Softisan 649, Mineral Oil, Aloe Extract.

PRINCIPAL DISPLAY PANEL

NDC 43553-4134-1

ConvaTec

ALOE VESTATM

Protective Barrier Spray 3

PROTECT

SKIN PROTECTANT

Shake before use

Soothes irritated skin

For weepy, denuded skin

Apply from any angle

Easy to remove

NET WT. 2.1 oz.(60g)

CSX1876A Case Order No. 413401